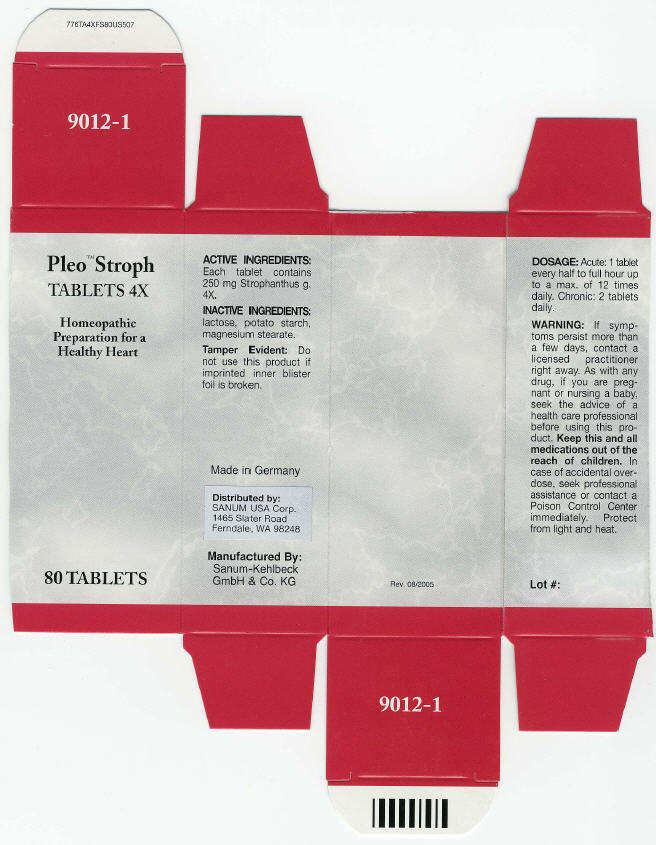 DRUG LABEL: Pleo Stroph
NDC: 60681-9012 | Form: TABLET
Manufacturer: Sanum Kehlbeck GmbH & Co. KG
Category: homeopathic | Type: HUMAN OTC DRUG LABEL
Date: 20091125

ACTIVE INGREDIENTS: strophanthus hispidus 4 [hp_X]/1 1
INACTIVE INGREDIENTS: lactose; Starch, Potato; Magnesium Stearate

Pleo™ Stroph
TABLETS 4X

Homeopathic Preparation for a Healthy Heart

80 TABLETS

ACTIVE INGREDIENTS

Each tablet contains 250 mg Strophanthus g. 4X.

INACTIVE INGREDIENTS

lactose, potato starch, magnesium stearate.

Tamper Evident

Do not use this product if imprinted inner blister foil is broken.

DOSAGE

Acute

1 tablet every half to full hour up to a max. of 12 times daily.

Chronic

2 tablets daily.

WARNING

If symptoms persist more than a few days, contact a licensed practitioner right away. As with any drug, if you are pregnant or nursing a baby, seek the advice of a health care professional before using this product.

KEEP OUT OF REACH OF CHILDREN

Keep this and all medications out of the reach of children. In case of accidental overdose, seek professional assistance or contact a Poison Control Center immediately.

STORAGE AND HANDLING

Protect from light and heat.

Made in Germany

Distributed by:
SANUM USA Corp.,
1465 Slater Road
Ferndale, WA 98248

Manufactured By:
SANUM-Kehlbeck
GmbH & Co. KG

Rev. 08/2005

PRINCIPAL DISPLAY PANEL - 80 Tablet Carton

Pleo™ Stroph
TABLETS 4X

Homeopathic
Preparation for a
Healthy Heart

80 TABLETS